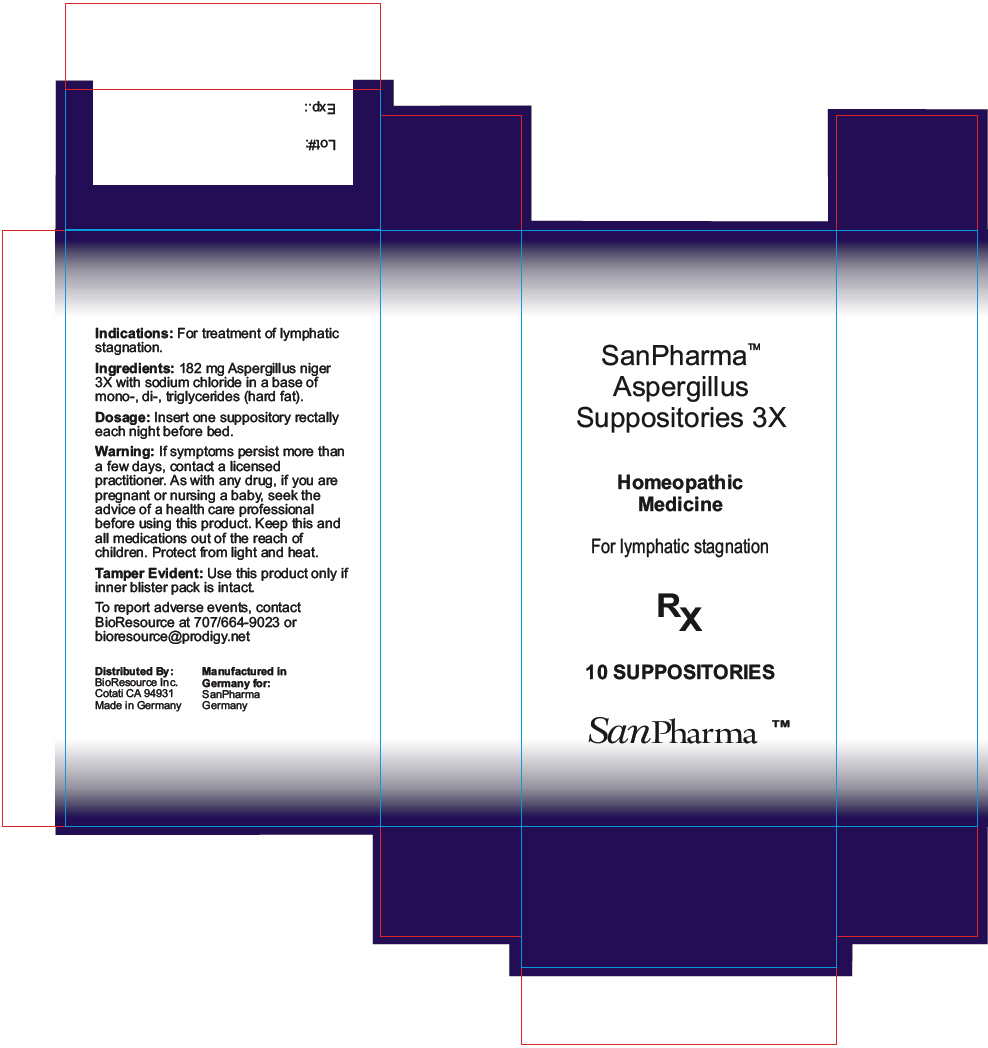 DRUG LABEL: Aspergillus
NDC: 54256-029 | Form: SUPPOSITORY
Manufacturer: BioResource Inc.
Category: homeopathic | Type: HUMAN OTC DRUG LABEL
Date: 20160129

ACTIVE INGREDIENTS: Aspergillus Niger Var. Niger 3 [hp_X]/1 1
INACTIVE INGREDIENTS: Fat, Hard; Sodium chloride

Aspergillus suppositories

Indications

PURPOSE

For treatment of lymphatic stagnation.

Ingredients

INACTIVE INGREDIENT

182 mg Aspergillus niger 3X with sodium chloride in a base of mono-, di-, triglycerides (hard fat).

Dosage

Insert one suppository rectally each night before bed.

Warning

If symptoms persist more than a few days, contact a licensed practitioner. As with any drug, if you are pregnant or nursing a baby, seek the advice of a health care professional before using this product.

KEEP OUT OF REACH OF CHILDREN

Keep this and all medications out of the reach of children. Protect from light and heat.

Tamper Evident

Use this product only if inner blister pack is intact.

To report adverse events, contact BioResource at 707/664-9023 or bioresource@prodigy.net

Distributed By:
BioResource Inc.
Cotati CA 94931

PRINCIPAL DISPLAY PANEL - 10 Suppository Blister Pack Box

SanPharma™
Aspergillus
Suppositories 3X

Homeopathic
Medicine

For lymphatic stagnation

RX

10 SUPPOSITORIES

SanPharma ™